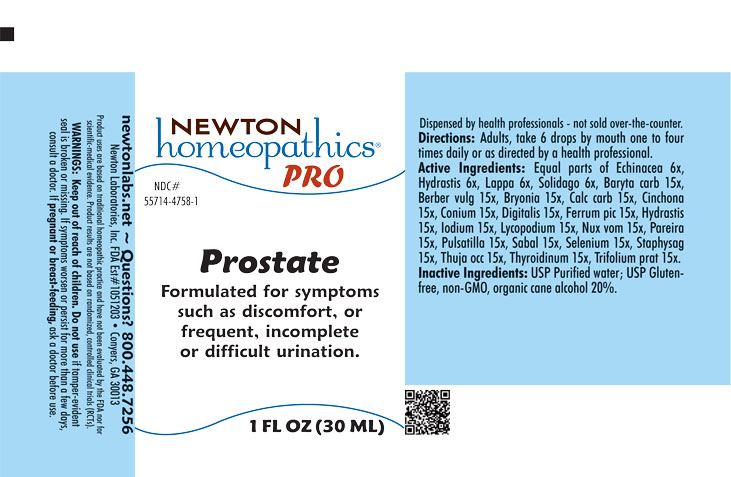 DRUG LABEL: Prostate
NDC: 55714-4758 | Form: LIQUID
Manufacturer: Newton Laboratories, Inc.
Category: homeopathic | Type: HUMAN OTC DRUG LABEL
Date: 20251203

ACTIVE INGREDIENTS: IODINE 15 [hp_X]/1 mL; THYROID, UNSPECIFIED 15 [hp_X]/1 mL; BARIUM CARBONATE 15 [hp_X]/1 mL; BERBERIS VULGARIS ROOT BARK 15 [hp_X]/1 mL; BRYONIA ALBA ROOT 15 [hp_X]/1 mL; OYSTER SHELL CALCIUM CARBONATE, CRUDE 15 [hp_X]/1 mL; CINCHONA OFFICINALIS BARK 15 [hp_X]/1 mL; CONIUM MACULATUM FLOWERING TOP 15 [hp_X]/1 mL; DIGITALIS 15 [hp_X]/1 mL; FERRIC PICRATE 15 [hp_X]/1 mL; GOLDENSEAL 15 [hp_X]/1 mL; LYCOPODIUM CLAVATUM SPORE 15 [hp_X]/1 mL; STRYCHNOS NUX-VOMICA SEED 15 [hp_X]/1 mL; CHONDRODENDRON TOMENTOSUM ROOT 15 [hp_X]/1 mL; ANEMONE PULSATILLA 15 [hp_X]/1 mL; SAW PALMETTO 15 [hp_X]/1 mL; SELENIUM 15 [hp_X]/1 mL; DELPHINIUM STAPHISAGRIA SEED 15 [hp_X]/1 mL; THUJA OCCIDENTALIS LEAFY TWIG 15 [hp_X]/1 mL; TRIFOLIUM PRATENSE FLOWER 15 [hp_X]/1 mL; ECHINACEA, UNSPECIFIED 6 [hp_X]/1 mL; ARCTIUM LAPPA ROOT 6 [hp_X]/1 mL; SOLIDAGO VIRGAUREA FLOWERING TOP 6 [hp_X]/1 mL
INACTIVE INGREDIENTS: WATER; ALCOHOL

Prostate 4758L

INDICATIONS & USAGE SECTION

Formulated for associated symptoms such as discomfort, or frequent, incomplete or difficult urination.

DOSAGE & ADMINISTRATION SECTION

Directions: Adults, take 6 drops by mouth one to four times daily or as directed by a health professional.

OTC - ACTIVE INGREDIENT SECTION

Equal parts of Echinacea 6x, Hydrastis canadensis 6x, Lappa major 6x, Solidago virgaurea 6x, Baryta carbonica 15x, Berberis vulgaris 15x, Bryonia 15x, Calcarea carbonica 15x, Cinchona officinalis 15x, Conium maculatum 15x, Digitalis purpurea 15x, Ferrum picricum 15x, Hydrastis canadensis 15x, Iodium 15x, Lycopodium clavatum 15x, Nux vomica 15x, Pareira brava 15x, Pulsatilla 15x, Sabal serrulata 15x, Selenium metallicum 15x, Staphysagria 15x, Thuja occidentalis 15x, Thyroidinum 15x, Trifolium pratense 15x.

OTC - PURPOSE SECTION

Formulated for associated symptoms such as discomfort, or frequent, incomplete or difficult urination.

INACTIVE INGREDIENT SECTION

USP Purified Water; USP Gluten-free, non-GMO, organic cane alcohol 20%.

QUESTIONS SECTION

newtonlabs.net – Questions? 800.448.7256

Newton Laboratories, Inc. FDA Est # 1051203 - Conyers, GA 30013

WARNINGS SECTION

WARNINGS: Keep out of reach of children. Do not use if tamper-evident seal is broken or missing. If symptoms worsen or persist for more than a few days, consult a doctor. If pregnant or breast-feeding, ask a doctor before use.

OTC - PREGNANCY OR BREAST FEEDING SECTION

If pregnant or breast-feeding, ask a doctor before use.

OTC - KEEP OUT OF REACH OF CHILDREN SECTION

Keep out of reach of children.